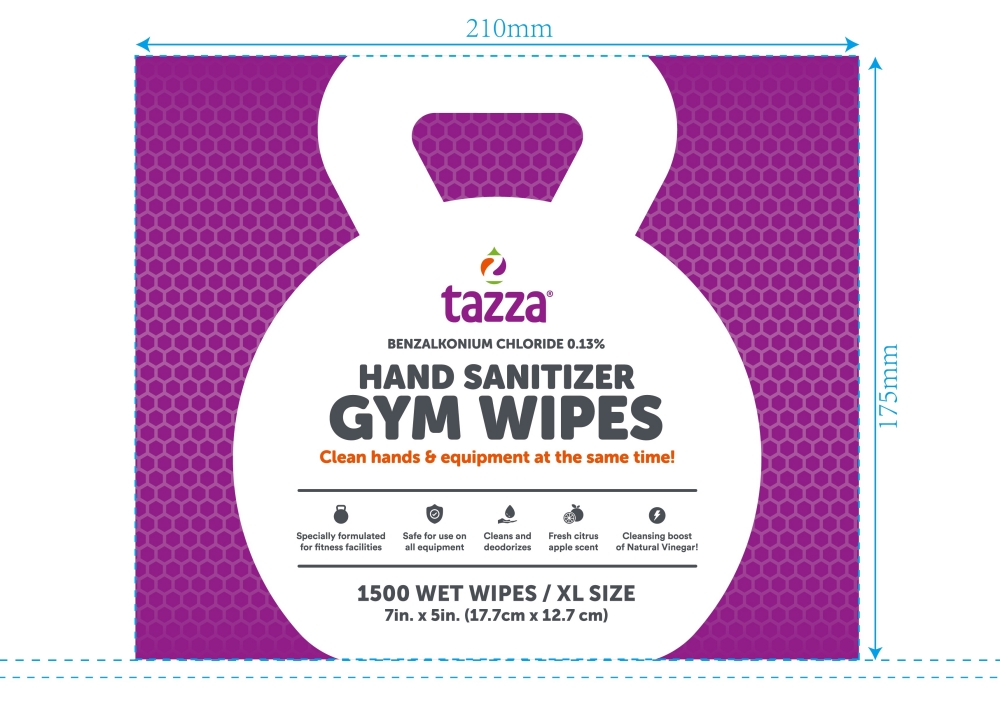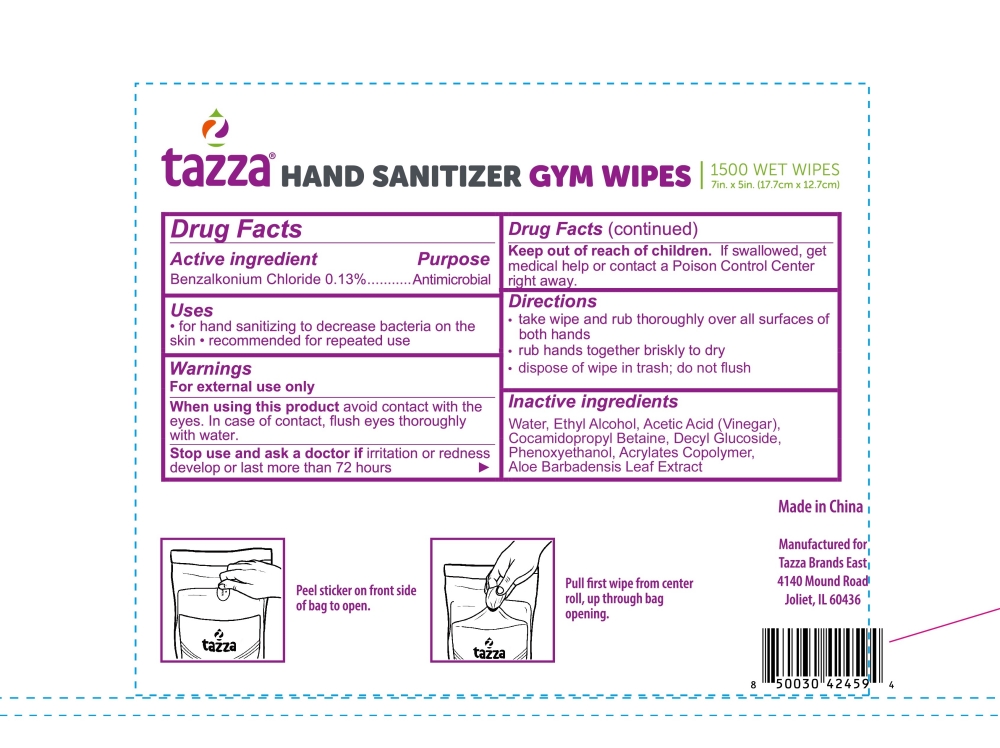 DRUG LABEL: Tazza Hand Sanitizer
NDC: 76370-0017 | Form: CLOTH
Manufacturer: Tazza Brands East Inc
Category: otc | Type: HUMAN OTC DRUG LABEL
Date: 20251217

ACTIVE INGREDIENTS: BENZALKONIUM CHLORIDE 0.13 g/100 mL
INACTIVE INGREDIENTS: ACETIC ACID; COCAMIDOPROPYL BETAINE; PHENOXYETHANOL; ALOE VERA LEAF; BUTYL ACRYLATE/METHYL METHACRYLATE/METHACRYLIC ACID COPOLYMER (18000 MW); WATER; ALCOHOL; DECYL GLUCOSIDE

76370-0017 Tazza Hand Sanitizer

Drug Facts

Active ingredient

Benzalkonium Chloride 0.13%

Purpose

Antimicrobial

Uses

- for hand sanitizing to decrease bacteria on the skin
- recommended for repeated use

Warnings

For external use only

WHEN USING

When using this productavoid contact with eyes. In case of contact, flush eyes thoroughly with water.

Stop use and ask a doctor ifirritation or redness develop or last more than 72 hours

Keep out of reach of children.If swallowed, get medical help or contact a Poison Control Center right away.

Directions

- take wipe and rub thoroughly over all surfaces of both hands
- rub hands together briskly to dry
- dispose of wipe in trash; do not flush

INACTIVE INGREDIENT

Inactive ingredientsWater, Ethyl Alcohol, Acetic Acid (Vinegar), Cocamidopropyl Betaine, Decyl Glucoside, Phenoxyethanol, Acrylates Copolymer, Aloe Barbadensis Leaf Extract,

Made in China

Manufactured for

Tazza Brands East

4140 Mound Road

Joliet, IL 60436

PACKAGE LABEL

1500 Wet Wipes / XL SIZE

7in x 5in (17.7cm x 12.7cm)
NDC: 76370-0017-0